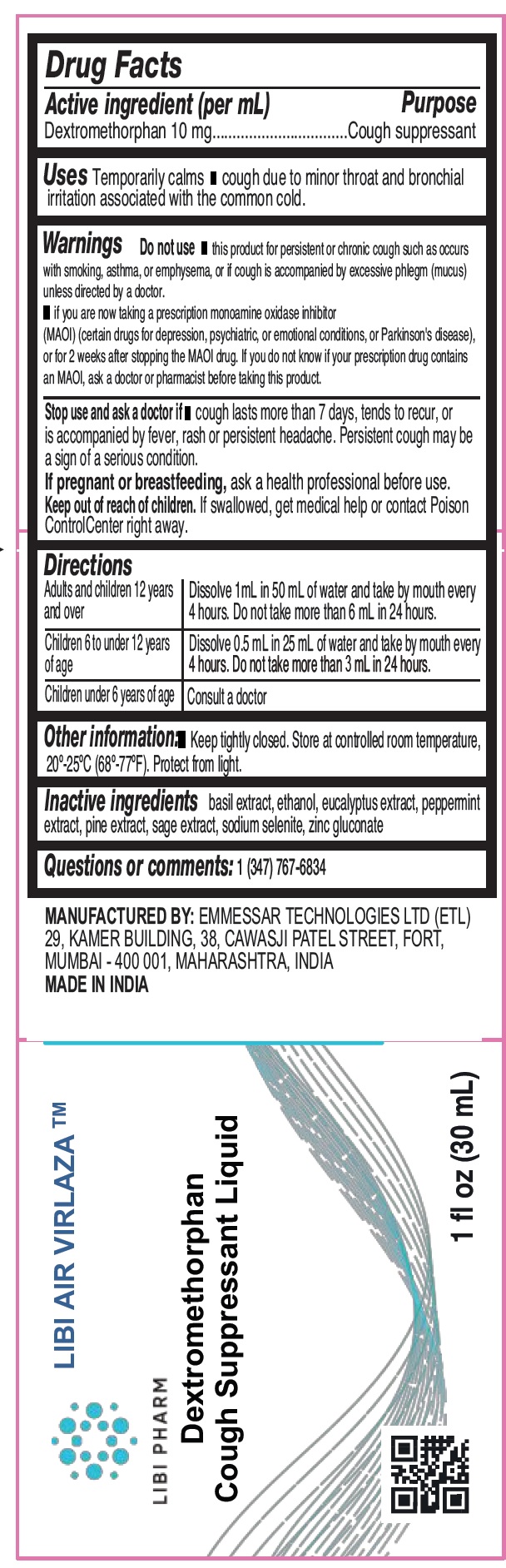 DRUG LABEL: LIBI AIR VIRLAZA Dextromethorphan Cough Suppressant
NDC: 84314-000 | Form: LIQUID
Manufacturer: Libi Pharm Ltd.
Category: otc | Type: HUMAN OTC DRUG LABEL
Date: 20250623

ACTIVE INGREDIENTS: DEXTROMETHORPHAN 10 mg/1 mL
INACTIVE INGREDIENTS: ALCOHOL; EUCALYPTUS GLOBULUS LEAF; PEPPERMINT; SODIUM SELENITE; ZINC GLUCONATE

LIBI AIR VIRLAZA Dextromethorphan Cough Suppressant Liquid

Active ingredient (per mL)

Dextromethorphan 10 mg

Purpose

Cough suppressant

Uses

Temporarily calms Ê cough due to minor throat and bronchial irritation associated with the common cold.

Warnings

Do not use

- this product for persistent or chronic cough such as occurs with smoking, asthma, or emphysema, or if cough is accompanied by excessive phlegm (mucus) unless directed by a doctor.
- if you are now taking a prescription monoamine oxidase inhibitor (MAOI) (certain drugs for depression, psychiatric, or emotional conditions, or Parkinson's disease), or for 2 weeks after stopping the MAOI drug. If you do not know if your prescription drug contains an MAOI, ask a doctor or pharmacist before taking this product.

Stop use and ask a doctor if

- cough lasts more than 7 days, tends to recur, or is accompanied by fever, rash or persistent headache. Persistent cough may be a sign of a serious condition.

If pregnant or breastfeeding,

ask a health professional before use.

Keep out of reach of children.

If swallowed, get medical help or contact Poison ControlCenter right away.

Directions

Adults and children 12 years and over | Dissolve 1mL in 50 mL of water and take by mouth every 4 hours. Do not take more than 6 mL in 24 hours.
Children 6 to under 12 years of age | Dissolve 0.5 mL in 25 mL of water and take by mouth every 4 hours. Do not take more than 3 mL in 24 hours.
Children under 6 years of age | Consult a doctor

Other information:

- Keep tightly closed. Store at controlled room temperature, 20°-25°C (68°-77°F). Protect from light.

Inactive ingredients

basil extract, ethanol, eucalyptus extract, peppermint extract, pine extract, sage extract, sodium selenite, zinc gluconate

Questions or comments:

1 (347) 767-6834